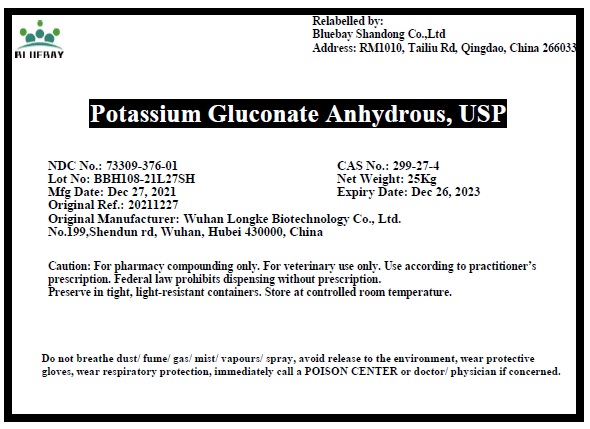 DRUG LABEL: Potassium Gluconate Anhydrous
NDC: 73309-376 | Form: POWDER
Manufacturer: BLUEBAY SHANDONG CO.,LTD
Category: other | Type: BULK INGREDIENT - ANIMAL DRUG
Date: 20220311

ACTIVE INGREDIENTS: POTASSIUM GLUCONATE 1 kg/1 kg

Potassium Gluconate Anhydrous